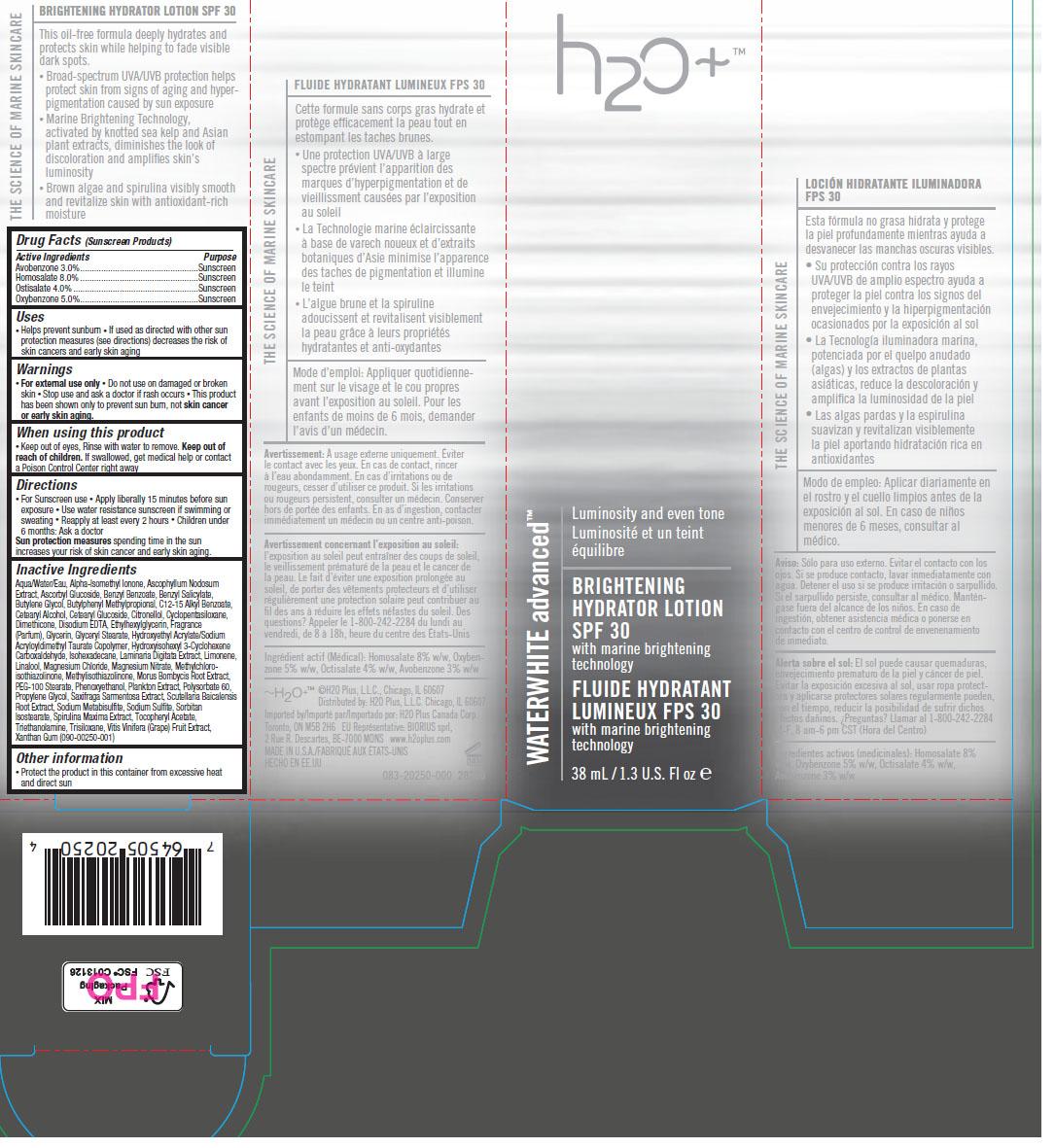 DRUG LABEL: WhiteWater Advanced Brightening
NDC: 65903-250 | Form: LOTION
Manufacturer: H2O PLUS
Category: otc | Type: HUMAN OTC DRUG LABEL
Date: 20110929

ACTIVE INGREDIENTS: Avobenzone 3 mL/100 mL; Homosalate 8 mL/100  mL; Octisalate 4 mL/100 mL; Oxybenzone 5 mL/100 mL
INACTIVE INGREDIENTS: water; ISOMETHYL-.ALPHA.-IONONE; ASCOPHYLLUM NODOSUM; BENZYL BENZOATE; BENZYL SALICYLATE; BUTYLENE GLYCOL; BUTYLPHENYL METHYLPROPIONAL; ALKYL (C12-15) BENZOATE; CETOSTEARYL ALCOHOL; CETEARYL GLUCOSIDE; CITRONELLOL ACETATE, (S)-; CYCLOMETHICONE 5; DIMETHICONE; EDETIC ACID; ETHYLHEXYLGLYCERIN; GLYCERIN; GLYCERYL MONOSTEARATE; SODIUM ACRYLATE/SODIUM ACRYLOYLDIMETHYLTAURATE COPOLYMER (4000000 MW); HYDROXYISOHEXYL 3-CYCLOHEXENE CARBOXALDEHYDE; ISOHEXADECANE; LAMINARIA DIGITATA; LIMONENE, (+)-; LINALOOL, (+/-)-; MAGNESIUM CHLORIDE; MAGNESIUM NITRATE; METHYLCHLOROISOTHIAZOLINONE; METHYLISOTHIAZOLINONE; MORUS AUSTRALIS ROOT; PEG-100 STEARATE; PHENOXYETHANOL; POLYSORBATE 60; PROPYLENE GLYCOL; SAXIFRAGA STOLONIFERA LEAF; SCUTELLARIA BAICALENSIS ROOT; SODIUM METABISULFITE; SODIUM SULFITE; POLYSORBATE 60; SPIRULINA MAXIMA; .ALPHA.-TOCOPHEROL ACETATE, DL-; TRIETHANOLAMINE HYDROCHLORIDE; TRISILOXANE; VITIS VINIFERA FLOWERING TOP; XANTHAN GUM

Drug Facts

ACTIVE INGREDIENT

Avobenzone 3.0%
Homosalate 8.0%
Octisalate 4.0%
Oxybenzone 5.0%

PURPOSE

Sunscreen
Sunscreen
Sunscreen
Sunscreen

WHEN USING

• Helps prevent sunburn
• If used as directed with other sun protection measures
(see directions) decreases the risk of skin cancers and early skin aging

WARNINGS

• For external use only • Do not use on damaged or broken skin
• Stop use and ask a doctor if rash occurs

Keep out of eyes, Rinse with water to remove. Keep out of reach of children.

If swallowed, get medical help or contact a Poison Control Center right away

DOSAGE AND ADMINISTRATION

• For Sunscreen use
• Apply liberally 15 minutes before sun exposure
• Use water resistance sunscreen if swimming or sweating
• Reapply at least every 2 hours
• Children under 6 months: Ask a doctor

STORAGE AND HANDLING

Protect the product in this container from excessive heat
and direct sun

INACTIVE INGREDIENT

Aqua/Water/Eau, Alpha-Isomethyl Ionone, Ascophyllum Nodosum Extract, Ascorbyl
Glucoside, Benzyl Benzoate, Benzyl Salicylate, Butylene Glycol, Butylphenyl
Methylpropional, C12-15 Alkyl Benzoate, Cetearyl Alcohol, Cetearyl Glucoside,
Citronellol, Cyclopentasiloxane, Dimethicone, Disodium EDTA, Ethylhexylglycerin,
Fragrance (Parfum), Glycerin, Glyceryl Stearate, Hydroxyethyl Acrylate/Sodium
Acryloyldimethyl Taurate Copolymer, Hydroxyisohexyl 3-Cyclohexene Carboxaldehyde,
Isohexadecane, Laminaria Digitata Extract, Limonene, Linalool, Magnesium Chloride,
Magnesium Nitrate, Methylchloroisothiazolinone, Methylisothiazolinone, Morus
Bombycis Root Extract, PEG-100 Stearate, Phenoxyethanol, Plankton Extract,
Polysorbate 60, Propylene Glycol, Saxifraga Sarmentosa Extract, Scutellaria
Baicalensis Root Extract, Sodium Metabisulfite, Sodium Sulfite, Sorbitan Isostearate,
Spirulina Maxima Extract, Tocopheryl Acetate, Triethanolamine, Trisiloxane, Vitis
Vinifera (Grape) Fruit Extract, Xanthan Gum

Image of carton label wwa250.jpg